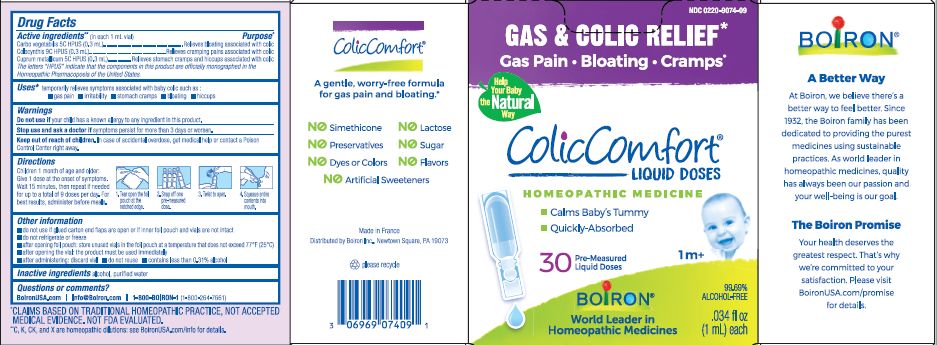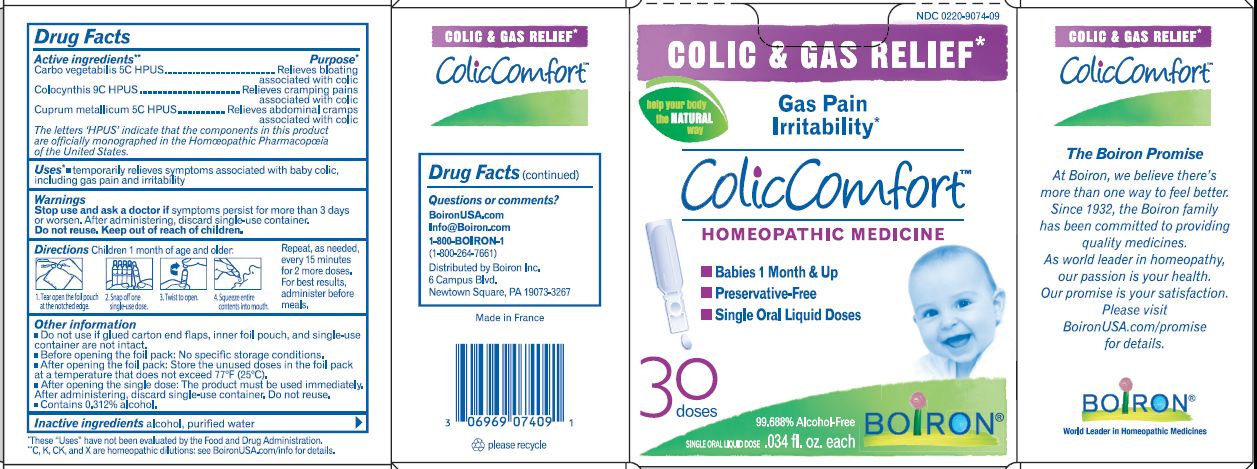 DRUG LABEL: ColicComfort
NDC: 0220-9074 | Form: LIQUID
Manufacturer: Boiron
Category: homeopathic | Type: HUMAN OTC DRUG LABEL
Date: 20240611

ACTIVE INGREDIENTS: ACTIVATED CHARCOAL 5 [hp_C]/1 1; COPPER 5 [hp_C]/1 1; CITRULLUS COLOCYNTHIS FRUIT 9 [hp_C]/1 1
INACTIVE INGREDIENTS: WATER

ColicComfort

ACTIVE INGREDIENT

Carbo vegetabilis 5C HPUS

Colocynthis 9C HPUS

Cuprum metallicum 5C HPUS

INDICATIONS AND USAGE

Temporarily relieves symptoms associated with baby colic such as gas pain, irritability, stomach cramps, bloating, hiccups

Do not use if your child has a known allergy to any ingredient in this product.

Do not use if glued carton end flaps are open or if inner foil pouch and vials are not intact

Do not refrigerate or freeze

Do not reuse

DOSAGE AND ADMINISTRATION

Children 1 month of age and older: Give 1 dose at the onset of symptoms, Wait 15 minutes, then repeate if needed for up to a total of 9 doses per day. For best results administer before meals.

Tear open the foil pouch at the notched edge, Snap off one pre-measured dose, twist open, squeeze entire contents into mouth.

INACTIVE INGREDIENT

alcohol, purified water

HOW SUPPLIED

30 doses of 0.34 fl. oz. each

PURPOSE

Carbo vegetabilis 5C HPUS .................relieves bloating associated with colic

Colocynthis 9C HPUS .....................relieves cramping pains associated with colic

Cuprum metallicum 5C HPUS ..........relieves abdominal cramps associated with colic

STORAGE AND HANDLING

After opening the foil pack: store the unused doses in the foil pack at a temperature that does noe exceed 77 F (25 C)

After opening the vial: the product must be used immediately

After administrating: discal vial

Questions or comments?

BoironUSA.com

Info@Boiron.com

1-800-BOIRON-1

(1-800-264-7661)

Distributed by Boiron Inc.

Stop use and ask a doctor if symptoms persist for more than 3 days or worsen.

Stop use and ask doctor if symptoms persist for more than 3 days or worsen.

Keep out of reach of children. In case of accidental overdose, get medical help or contact a Poison Control Center right away.

PREGNANCY OR BREAST FEEDING

NA

WHEN USING

After administering, discard single use container.

Do not reuse.

After opening the single dose, the product must be used immediately. After administering, discard single use container. Do not reuse.

contains 0.31% alcohol

The letters "HPUS" indicate that the components in this product are officially monographed in the Homeopathic Pharmacopoeia of the United States.

*CLAIMS BASED ON TRADITIONAL HOMEOPATHIC PRACTICE NOT ACCEPTED MEDICAL EVIDENCE. NOT FDA EVALUATED.
**C,K,CK, and X are homeopathic dilutions: see BoironUSA.com/info for details.